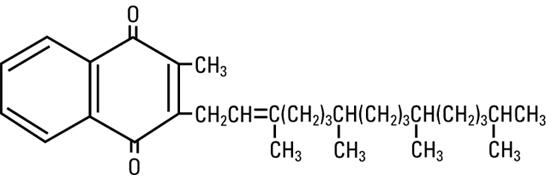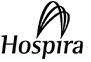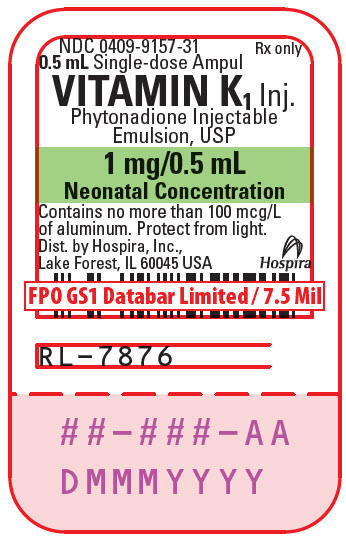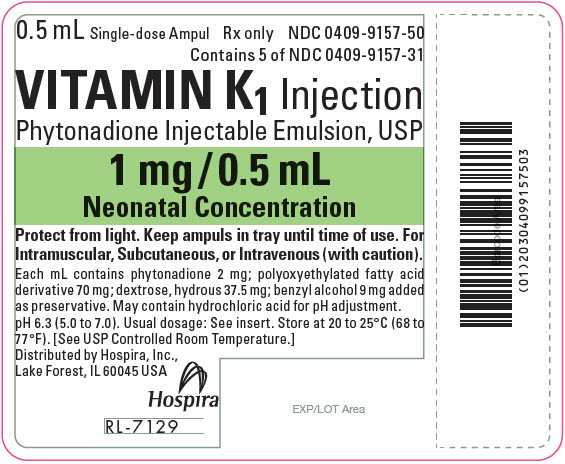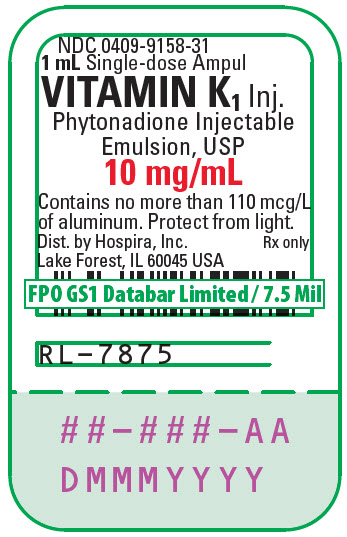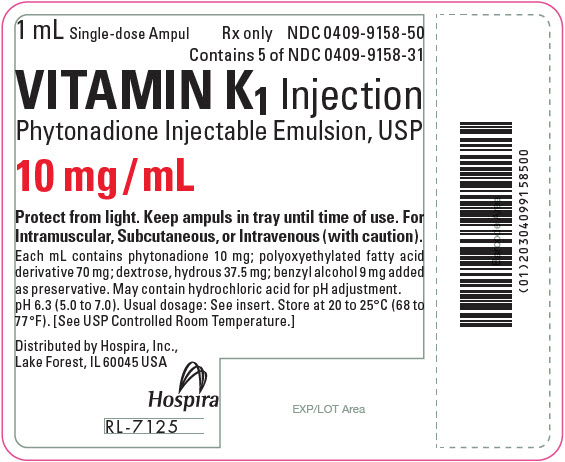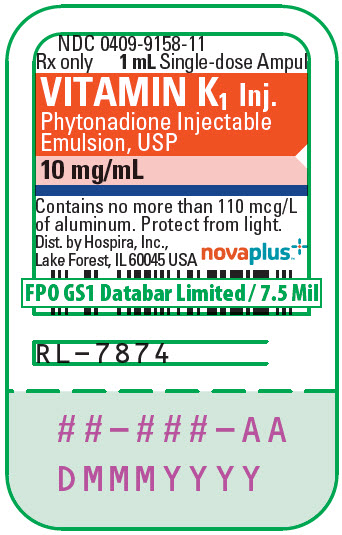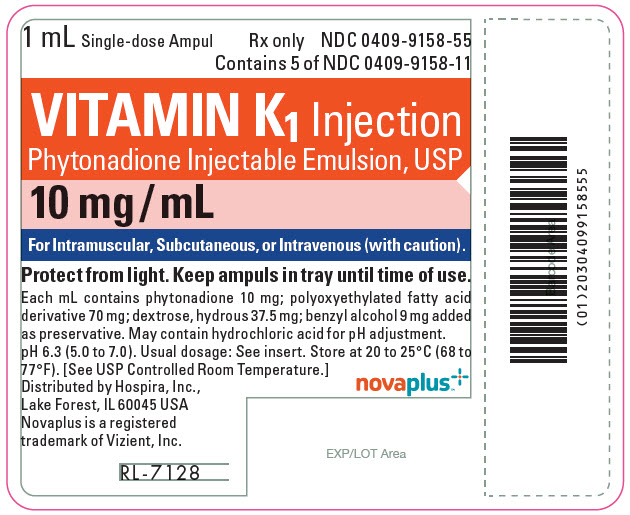 DRUG LABEL: Vitamin K1
NDC: 0409-9157 | Form: INJECTION, EMULSION
Manufacturer: Hospira, Inc.
Category: prescription | Type: HUMAN PRESCRIPTION DRUG LABEL
Date: 20250924

ACTIVE INGREDIENTS: PHYTONADIONE 2 mg/1 mL
INACTIVE INGREDIENTS: POLYOXYL 35 CASTOR OIL 70 mg/1 mL; DEXTROSE MONOHYDRATE 37.5 mg/1 mL; WATER; BENZYL ALCOHOL 9 mg/1 mL; HYDROCHLORIC ACID

HIGHLIGHTS OF PRESCRIBING INFORMATION

These highlights do not include all the information needed to use VITAMIN K1 INJECTION safely and effectively. See full prescribing information for VITAMIN K1 INJECTION.
VITAMIN K1 INJECTION (Phytonadione Injectable Emulsion, USP), for intravenous, intramuscular, and subcutaneous use.
Initial U.S. Approval: 1960

WARNING: HYPERSENSITIVITY REACTIONS WITH INTRAVENOUS AND INTRAMUSCULAR USE

See full prescribing information for complete boxed warning.

Fatal hypersensitivity reactions, including anaphylaxis, have occurred during and immediately after INTRAVENOUS and INTRAMUSCULAR injection of Vitamin K1 Injection. Reactions have occurred despite dilution to avoid rapid infusion and upon first and subsequent doses. Avoid the intravenous and intramuscular routes of administration unless the subcutaneous route is not feasible and the serious risk is justified. (5.1)

1 INDICATIONS AND USAGE

Vitamin K1 Injection is a vitamin K replacement indicated for the treatment of the following coagulation disorders which are due to faulty formation of factors II, VII, IX and X when caused by vitamin K deficiency or interference with vitamin K activity.

- Anticoagulant-induced hypoprothrombinemia deficiency caused by coumarin or indanedione derivatives. (1.1)
- Hypoprothrombinemia due to antibacterial therapy. (1.1)
- Hypoprothrombinemia secondary to factors limiting absorption or synthesis of vitamin K, e.g., obstructive jaundice, biliary fistula, sprue, ulcerative colitis, celiac disease, intestinal resection, cystic fibrosis of the pancreas, and regional enteritis. (1.1)
- Other drug-induced hypoprothrombinemia where it is definitely shown that the result is due to interference with vitamin K metabolism, e.g., salicylates. (1.1)

Vitamin K1 Injection is indicated for prophylaxis and treatment of vitamin K-deficiency bleeding in neonates. (1.2)

2 DOSAGE AND ADMINISTRATION

- Administer Vitamin K1 Injection by the subcutaneous route, whenever possible. (2.1)
- When intravenous administration is unavoidable, inject the drug very slowly, not exceeding 1 mg per minute. (2.1)

3 DOSAGE FORMS AND STRENGTHS

Injection: 1 mg/0.5 mL and 10 mg/mL single-dose ampuls. (3)

4 CONTRAINDICATIONS

Hypersensitivity to any component of this medication. (4)

5 WARNINGS AND PRECAUTIONS

- Risk of Serious Adverse Reactions in Infants due to Benzyl Alcohol Preservative: Use benzyl alcohol-free phytonadione formulations in neonates and infants, if available. (5.2)
- Cutaneous Reactions: May occur with parenteral use. Discontinue drug and manage medically. (5.3)

6 ADVERSE REACTIONS

Most common adverse reactions are cyanosis, diaphoresis, dizziness, dysgeusia, dyspnea, flushing, hypotension and tachycardia. (6)

To report SUSPECTED ADVERSE REACTIONS, contact Pfizer Inc. at 1‑800‑438‑1985 or FDA at 1-800-FDA-1088 or www.fda.gov/medwatch.

7 DRUG INTERACTIONS

Anticoagulants: May induce temporary resistance to prothrombin-depressing anticoagulants. (7)

8 USE IN SPECIFIC POPULATIONS

- Pregnancy: If available, use a preservative-free phytonadione formulation in pregnant women. (8.1)
- Lactation: If available, use a preservative-free phytonadione formulation in lactating women. (8.2)
- Pediatric Use: The safety and effectiveness of Vitamin K1 Injection in pediatric patients from 6 months to 17 years have not been established. (8.4)

FULL PRESCRIBING INFORMATION

WARNING: HYPERSENSITIVITY REACTIONS WITH INTRAVENOUS AND INTRAMUSCULAR USE

Fatal hypersensitivity reactions, including anaphylaxis, have occurred during and immediately after intravenous and intramuscular injection of Vitamin K1 Injection. Reactions have occurred despite dilution to avoid rapid intravenous infusion and upon first dose. Avoid the intravenous and intramuscular routes of administration unless the subcutaneous route is not feasible and the serious risk is justified [see Warnings and Precautions (5.1)].

1 INDICATIONS AND USAGE

1.1 Treatment of Hypoprothrombinemia Due to Vitamin K Deficiency or Interference

Vitamin K1 Injection is indicated for the treatment of the following coagulation disorders which are due to faulty formation of factors II, VII, IX and X when caused by vitamin K deficiency or interference with vitamin K activity:

- anticoagulant-induced hypoprothrombinemia caused by coumarin or indanedione derivatives;
- hypoprothrombinemia due to antibacterial therapy;
- hypoprothrombinemia secondary to factors limiting absorption or synthesis of vitamin K, e.g., obstructive jaundice, biliary fistula, sprue, ulcerative colitis, celiac disease, intestinal resection, cystic fibrosis of the pancreas, and regional enteritis;
- other drug-induced hypoprothrombinemia where it is definitely shown that the result is due to interference with vitamin K metabolism, e.g., salicylates.

1.2 Prophylaxis and Treatment of Vitamin K-Deficiency Bleeding in Neonates

Vitamin K1 Injection is indicated for prophylaxis and treatment of vitamin K-deficiency bleeding in neonates.

2 DOSAGE AND ADMINISTRATION

2.1 Dosing Considerations

Whenever possible, administer Vitamin K1 Injection by the subcutaneous route [see Boxed Warning]. When intravenous administration is unavoidable, inject the drug very slowly, not exceeding 1 mg per minute [see Warnings and Precautions (5.1)].

Monitor international normalized ratio (INR) regularly and as clinical conditions indicate. Use the lowest effective dose of Vitamin K1 Injection.

The coagulant effects of Vitamin K1 Injection are not immediate; improvement of INR may take 1 to 8 hours. Interim use of whole blood or component therapy may also be necessary if bleeding is severe.

Whenever possible, administer benzyl alcohol-free phytonadione formulations in pediatric patients [see Warnings and Precautions (5.2), Use in Specific Populations (8.4)].

When Vitamin K1 Injection is used to correct excessive anticoagulant-induced hypoprothrombinemia, anticoagulant therapy still being indicated, the patient is again faced with the clotting hazards existing prior to starting the anticoagulant therapy. Vitamin K1 Injection is not a clotting agent, but overzealous therapy with Vitamin K1 Injection may restore conditions which originally permitted thromboembolic phenomena. Dosage should be kept as low as possible, and INR should be checked regularly as clinical conditions indicate.

2.2 Recommended Dosage for Coagulation Disorders from Vitamin K Deficiency or Interference

The recommended dosage of Vitamin K1 Injection is based on whether the hypoprothrombinemia is anticoagulant-induced (e.g., due to coumarin or indanedione derivatives) or non-anticoagulant-induced (e.g., due to antibiotics; salicylates or other drugs; factors limiting absorption or synthesis) as follows:

- Anticoagulant-Induced Hypoprothrombinemia: Vitamin K1 Injection 2.5 mg to 10 mg or more subcutaneously, intramuscularly, or intravenously. Up to 25 mg to 50 mg may be administered as a single dose.

Repeated large doses of Vitamin K1 Injection are not warranted in liver disease if the initial response is unsatisfactory. Failure to respond to Vitamin K1 Injection may indicate that the condition being treated is inherently unresponsive to Vitamin K1 Injection.

- Hypoprothrombinemia Due to Other Causes (Non-Anticoagulation-Induced Hypoprothrombinemia): Vitamin K1 Injection 2.5 mg to 25 mg or more intravenously, intramuscularly, or subcutaneously. Up to 50 mg may be administered as a single dose.

Evaluate INR after 6 to 8 hours, and repeat dose if INR remains prolonged. Modify subsequent dosage (amount and frequency) based on the INR or clinical condition.

2.3 Recommended Dosage for Prophylaxis and Treatment of Vitamin K Deficiency Bleeding in Neonates

Prophylaxis of Vitamin K-Deficiency Bleeding in Neonates

The recommended dosage of Vitamin K1 Injection is 0.5 mg to 1 mg within one hour of birth for a single dose.

Treatment of Vitamin K Deficiency Bleeding in Neonates

The recommended dosage of Vitamin K1 Injection is 1 mg given either subcutaneously or intramuscularly. Consider higher doses if the mother has been receiving oral anticoagulants.

A failure to respond (shortening of the INR in 2 to 4 hours) may indicate another diagnosis or coagulation disorder.

2.4 Directions for Dilution

Dilute Vitamin K1 Injection with 0.9% Sodium Chloride Injection, 5% Dextrose Injection, or 5% Dextrose and Sodium Chloride Injection. Avoid use of other diluents that may contain benzyl alcohol, which can cause serious toxicity in newborns or low birth weight infants [see Warnings and Precautions (5.2), Use in Specific Populations (8.4)].

When diluted, start administration of Vitamin K1 Injection immediately after dilution. Discard unused portions of diluted solution as well as unused contents of the ampul.

Protect Vitamin K1 Injection from light at all times.

Parenteral drug products should be inspected visually for particulate matter and discoloration prior to administration, whenever solution and container permit.

3 DOSAGE FORMS AND STRENGTHS

Injection: 1 mg/0.5 mL and 10 mg/mL single-dose ampuls.

4 CONTRAINDICATIONS

Hypersensitivity to phytonadione or any other component of this medication [see Warnings and Precautions (5.1)].

5 WARNINGS AND PRECAUTIONS

5.1 Hypersensitivity Reactions

Fatal and severe hypersensitivity reactions, including anaphylaxis, have occurred with intravenous or intramuscular administration of Vitamin K1 Injection. Reactions have occurred despite dilution to avoid rapid intravenous infusion and upon first dose. These reactions have included shock, cardiorespiratory arrest, flushing, diaphoresis, chest pain, tachycardia, cyanosis, weakness, and dyspnea. Administer Vitamin K1 Injection subcutaneously whenever feasible. Avoid the intravenous and intramuscular routes of administration unless the subcutaneous route is not feasible and the serious risk is justified [see Dosage and Administration (2.1)].

5.2 Risk of Serious Adverse Reaction in Infants due to Benzyl Alcohol Preservative

Use benzyl alcohol-free phytonadione formulations in neonates and infants, if available. Serious and fatal adverse reactions including “gasping syndrome” can occur in neonates and infants treated with benzyl alcohol‑preserved drugs, including Vitamin K1 Injection. The “gasping syndrome” is characterized by central nervous system depression, metabolic acidosis, and gasping respirations.

When prescribing Vitamin K1 Injection in infants, consider the combined daily metabolic load of benzyl alcohol from all sources including Vitamin K1 Injection (contains 9 mg of benzyl alcohol per mL) and other drugs containing benzyl alcohol. The minimum amount of benzyl alcohol at which serious adverse reactions may occur is not known [see Use in Specific Populations (8.1, 8.2 and 8.4)].

5.3 Cutaneous Reactions

Parenteral administration of vitamin K replacements (including Vitamin K1 Injection) may cause cutaneous reactions. Reactions have included eczematous reactions, scleroderma-like patches, urticaria, and delayed-type hypersensitivity reactions. Time of onset ranged from 1 day to a year after parenteral administration. Discontinue Vitamin K1 Injection for skin reactions and institute medical management.

5.4 Aluminum Toxicity

WARNING: This product contains aluminum that may be toxic. Aluminum may reach toxic levels with prolonged parenteral administration if kidney function is impaired. Premature neonates are particularly at risk because their kidneys are immature, and they require large amounts of calcium and phosphate solutions, which contain aluminum.

Research indicates that patients with impaired kidney function, including premature neonates, who receive parenteral levels of aluminum at greater than 4 to 5 mcg/kg/day accumulate aluminum at levels associated with central nervous system and bone toxicity. Tissue loading may occur at even lower rates of administration.

6 ADVERSE REACTIONS

The following serious adverse reactions are described elsewhere in the labeling:

- Hypersensitivity Reactions [see Warnings and Precautions (5.1)]
- Cutaneous Reactions [see Warnings and Precautions (5.3)]

6.1 Clinical Trials Experience

Because clinical trials are conducted under widely varying conditions, adverse reaction rates observed in the clinical trials of a drug cannot be directly compared to rates in the clinical trials of another drug and may not reflect the rates observed in practice.

6.2 Postmarketing Experience

The following adverse reactions have been identified during post-approval use of Vitamin K1 Injection. Because these reactions were reported voluntarily from a population of uncertain size, it is not always possible to reliably estimate their frequency or establish a causal relationship to drug exposure.

Cardiac Disorders: Tachycardia, hypotension.

General Disorders and Administration Site Conditions: Generalized flushing; pain, swelling, and tenderness at injection site.

Hepatobiliary Disorders: Hyperbilirubinemia.

Immune System Disorders: Fatal hypersensitivity reactions, anaphylactic reactions.

Neurologic: Dysgeusia, dizziness.

Pulmonary: Dyspnea.

Skin and Subcutaneous Tissue Disorders: Erythema, pruritic plaques, scleroderma-like lesions, erythema perstans.

Vascular: Cyanosis.

7 DRUG INTERACTIONS

Anticoagulants

Vitamin K1 Injection may induce temporary resistance to prothrombin-depressing anticoagulants, especially when larger doses of Vitamin K1 Injection are used. Should this occur, higher doses of anticoagulant therapy may be needed when resuming anticoagulant therapy, or a change in therapy to a different class of anticoagulant may be necessary (i.e., heparin sodium).

Vitamin K1 Injection does not affect the anticoagulant action of heparin.

8 USE IN SPECIFIC POPULATIONS

8.1 Pregnancy

Risk Summary

Vitamin K1 Injection contains benzyl alcohol, which has been associated with gasping syndrome in neonates. The preservative benzyl alcohol can cause serious adverse events and death when administered intravenously to neonates and infants. If Vitamin K1 Injection is needed during pregnancy, consider using a benzyl alcohol-free phytonadione formulation [see Warnings and Precautions (5.2), Use in Specific Populations (8.4)].

Published studies with the use of phytonadione during pregnancy have not reported a clear association with phytonadione and adverse developmental outcomes [see Data]. There are maternal and fetal risks associated with vitamin K deficiency during pregnancy [see Clinical Considerations]. Animal reproduction studies have not been conducted with phytonadione.

The estimated background risk for the indicated population is unknown. All pregnancies have a background risk of birth defect, loss, or other adverse outcomes. In the U.S. general population, the estimated background risk of major birth defects and miscarriage in clinically recognized pregnancies is 2-4% and 15-20%, respectively.

Clinical Considerations

Disease-associated Maternal and/or Embryo/Fetal Risk

Pregnant women with vitamin K deficiency hypoprothrombinemia may be at an increased risk for bleeding diatheses during pregnancy and hemorrhagic events at delivery. Subclinical maternal vitamin K deficiency during pregnancy has been implicated in rare cases of fetal intracranial hemorrhage.

Data

Human Data

Phytonadione has been measured in cord blood of infants whose mothers were treated with phytonadione during pregnancy in concentrations lower than seen in maternal plasma. Administration of vitamin K1 to pregnant women shortly before delivery increased both maternal and cord blood concentrations. Published data do not report a clear association with phytonadione and adverse maternal or fetal outcomes when used during pregnancy. However, these studies cannot definitively establish the absence of any risk because of methodologic limitations including small sample size and lack of blinding.

Animal Data

In pregnant rats receiving vitamin K1 orally, fetal plasma and liver concentrations increased following administration, supporting placental transfer.

8.2 Lactation

Risk Summary

Vitamin K1 Injection contains benzyl alcohol. If available, a preservative-free phytonadione formulation is recommended when Vitamin K1 Injection is needed during lactation [see Warnings and Precautions (5.2), Use in Specific Populations (8.4)].

Phytonadione is present in breastmilk. There are no data on the effects of Vitamin K1 Injection on the breastfed child or on milk production. The developmental and health benefits of breastfeeding should be considered along with the clinical need for Vitamin K1 Injection and any potential adverse effects on the breastfed child from Vitamin K1 Injection or from the underlying maternal condition.

8.4 Pediatric Use

The safety and effectiveness of Vitamin K1 Injection for prophylaxis and treatment of vitamin K deficiency have been established in neonates. Use of phytonadione injection for prophylaxis and treatment of vitamin K deficiency is based on published clinical studies.

Serious adverse reactions including fatal reactions and the “gasping syndrome” occurred in premature neonates and infants in the intensive care unit who received drugs containing benzyl alcohol as a preservative. In these cases, benzyl alcohol dosages of 99 to 234 mg/kg/day produced high levels of benzyl alcohol and its metabolites in the blood and urine (blood levels of benzyl alcohol were 0.61 to 1.378 mmol/L). Additional adverse reactions included gradual neurological deterioration, seizures, intracranial hemorrhage, hematologic abnormalities, skin breakdown, hepatic and renal failure, hypotension, bradycardia, and cardiovascular collapse. Preterm, low birth weight infants may be more likely to develop these reactions because they may be less able to metabolize benzyl alcohol.

When prescribing Vitamin K1 Injection in infants consider the combined daily metabolic load of benzyl alcohol from all sources including Vitamin K1 Injection (Vitamin K1 Injection contains 9 mg of benzyl alcohol per mL) and other drugs containing benzyl alcohol. The minimum amount of benzyl alcohol at which serious adverse reactions may occur is not known [see Warnings and Precautions (5.2)].

Whenever possible, use preservative-free phytonadione formulations in neonates. The preservative benzyl alcohol has been associated with serious adverse events and death in pediatric patients. Premature and low birth weight infants may be more likely to develop toxicity.

10 OVERDOSAGE

Hemolysis, jaundice, and hyperbilirubinemia in newborns, particularly in premature infants, may result from Vitamin K1 Injection overdose.

11 DESCRIPTION

Phytonadione is a vitamin K replacement, which is a clear, yellow to amber, viscous, odorless or nearly odorless liquid. It is insoluble in water, soluble in chloroform and slightly soluble in ethanol. It has a molecular weight of 450.70.

Phytonadione is 2-methyl-3-phytyl-1, 4-naphthoquinone. Its empirical formula is C31H46O2 and its molecular structure is:

Vitamin K1 Injection (Phytonadione Injectable Emulsion, USP) is a yellow, sterile, nonpyrogenic aqueous dispersion available for injection by the intravenous, intramuscular and subcutaneous routes. Vitamin K1 Injection is available in 1 mg (1 mg/0.5 mL) and 10 mg (10 mg/mL) single-dose ampuls. Each milliliter contains phytonadione 2 mg or 10 mg, polyoxyethylated fatty acid derivative 70 mg, dextrose, hydrous 37.5 mg in water for injection; benzyl alcohol 9 mg added as preservative. May contain hydrochloric acid for pH adjustment. pH is 6.3 (5.0 to 7.0). Phytonadione is oxygen sensitive.

12 CLINICAL PHARMACOLOGY

12.1 Mechanism of Action

Vitamin K1 Injection aqueous dispersion of vitamin K1 for parenteral injection, possesses the same type and degree of activity as does naturally-occurring vitamin K, which is necessary for the production via the liver of active prothrombin (factor II), proconvertin (factor VII), plasma thromboplastin component (factor IX), and Stuart factor (factor X). Vitamin K is an essential cofactor for a microsomal enzyme that catalyzes the post‑translational carboxylation of multiple, specific, peptide-bound glutamic acid residues in inactive hepatic precursors of factors II, VII, IX, and X. The resulting gamma-carboxy-glutamic acid residues convert the precursors into active coagulation factors that are subsequently secreted by liver cells into the blood.

In normal animals and humans, phytonadione is virtually devoid of activity. However, in animals and humans deficient in vitamin K, the pharmacological action of vitamin K is related to its normal physiological function, that is, to promote the hepatic biosynthesis of vitamin K dependent clotting factors.

12.2 Pharmacodynamics

The action of the aqueous dispersion, when administered intravenously, is generally detectable within an hour or two and hemorrhage is usually controlled within 3 to 6 hours. A normal INR may often be obtained in 12 to 14 hours.

12.3 Pharmacokinetics

Absorption

Phytonadione is readily absorbed following intramuscular administration.

Distribution

After absorption, phytonadione is initially concentrated in the liver, but the concentration declines rapidly. Very little vitamin K accumulates in tissues.

Elimination

Little is known about the metabolic fate of vitamin K. Almost no free unmetabolized vitamin K appears in bile or urine.

13 NONCLINICAL TOXICOLOGY

13.1 Carcinogenesis, Mutagenesis, Impairment of Fertility

Studies of carcinogenicity, genotoxicity or impairment of fertility have not been conducted with phytonadione.

16 HOW SUPPLIED/STORAGE AND HANDLING

Vitamin K1 Injection (Phytonadione Injectable Emulsion, USP) is a yellow, sterile, nonpyrogenic aqueous dispersion and is supplied as follows:

Unit of Sale | Concentration
NDC 0409-9157-01 Bundle of 5 clamcells containing 5 single-dose ampuls | 1 mg/0.5 mL
NDC 0409-9158-01 Bundle of 5 clamcells containing 5 single-dose ampuls | 10 mg/mL

Store at 20°C to 25°C (68°F to 77°F). [See USP Controlled Room Temperature.]

Protect from light. Keep ampuls in tray until time of use.

17 PATIENT COUNSELING INFORMATION

Inform the patient of the following important risks of Vitamin K1 Injection:

Serious Hypersensitivity Reactions

Advise the patient and caregivers to immediately report signs of hypersensitivity after receiving Vitamin K1 Injection [see Warnings and Precautions (5.1)].

Risk of Gasping Syndrome Due to Benzyl Alcohol

Advise the patient and caregivers of the risk of gasping syndrome associated with the use of products that contain benzyl alcohol (including Vitamin K1 Injection) in neonates, infants, and pregnant women [see Warnings and Precautions (5.2)].

Cutaneous Reactions

Advise the patient and caregivers to report the occurrence of new rashes after receiving Vitamin K1 Injection. These reactions may be delayed for up to a year after treatment [see Warnings and Precautions (5.3)].

This product’s labeling may have been updated. For the most recent prescribing information, please visit www.pfizer.com.

Distributed by Hospira, Inc., Lake Forest, IL 60045 USA

LAB-1141-3.0

PRINCIPAL DISPLAY PANEL - 0.5 mL Ampul Label - RL-7876

NDC 0409-9157-31

0.5 mL Single-dose Ampul

Rx only

VITAMIN K1 Inj.
Phytonadione Injectable
Emulsion, USP

1 mg/0.5 mL
Neonatal Concentration

Contains no more than 100 mcg/L
of aluminum. Protect from light.

Dist. by Hospira, Inc.,
Lake Forest, IL 60045 USA

Hospira

RL-7876

##-###-AA
DMMMYYYY

PRINCIPAL DISPLAY PANEL - 0.5 mL Ampul Tray Label - RL-7129

0.5 mL Single-dose Ampul

Rx only NDC 0409-9157-50
Contains 5 of NDC 0409-9157-31

VITAMIN K1 Injection
Phytonadione Injectable Emulsion, USP

1 mg/0.5 mL
Neonatal Concentration

Protect from light. Keep ampuls in tray until time of use. For
Intramuscular, Subcutaneous, or Intravenous (with caution).

Each mL contains phytonadione 2 mg; polyoxyethylated fatty acid
derivative 70 mg; dextrose, hydrous 37.5 mg; benzyl alcohol 9 mg added
as preservative. May contain hydrochloric acid for pH adjustment.
pH 6.3 (5.0 to 7.0). Usual dosage: See insert. Store at 20 to 25°C (68 to
77°F). [See USP Controlled Room Temperature.]

Distributed by Hospira, Inc.,
Lake Forest, IL 60045 USA

Hospira

RL-7129

PRINCIPAL DISPLAY PANEL - 1 mL Ampul Label - RL-7875

NDC 0409-9158-31

1 mL only Single-dose Ampul

VITAMIN K1 Inj.

Phytonadione Injectable
Emulsion, USP

10 mg/mL

Contains no more than 110 mcg/L
of aluminum. Protect from light.

Dist. by Hospira, Inc.
Lake Forest, IL 60045 USA

Rx only

RL-7875

##-###-AA
DMMMYYYY

PRINCIPAL DISPLAY PANEL - 1 mL Ampul Tray Label - RL-7125

1 mL Single-dose Ampul

Rx only NDC 0409-9158-50
Contains 5 of NDC 0409-9158-31

VITAMIN K1 Injection
Phytonadione Injectable Emulsion, USP

10 mg/mL

Protect from light. Keep ampuls in tray until time of use. For
Intramuscular, Subcutaneous, or Intravenous (with caution).

Each mL contains phytonadione 10 mg; polyoxyethylated fatty acid
derivative 70 mg; dextrose, hydrous 37.5 mg; benzyl alcohol 9 mg added
as preservative. May contain hydrochloric acid for pH adjustment.
pH 6.3 (5.0 to 7.0). Usual dosage: See insert. Store at 20 to 25°C (68 to
77°F). [See USP Controlled Room Temperature.]

Distributed by Hospira, Inc.,
Lake Forest, IL 60045 USA

Hospira

RL-7125

PRINCIPAL DISPLAY PANEL - 1 mL Ampul Label - RL-7874

NDC 0409-9158-11
Rx only
1 mL Single-dose Ampul

VITAMIN K1 Inj.
Phytonadione Injectable
Emulsion, USP
10 mg/mL

Contains no more than 110 mcg/L
of aluminum. Protect from light.
Dist. by Hospira, Inc.,
Lake Forest, IL 60045 USA

novaplus™

RL-7874

##-###-AA
DMMMYYYY

PRINCIPAL DISPLAY PANEL - 1 mL Ampul Tray Label - RL-7128

1 mL Single-dose Ampul
Rx only
NDC 0409-9158-55
Contains 5 of NDC 0409-9158-11

VITAMIN K1 Injection
Phytonadione Injectable Emulsion, USP

10 mg/mL

For Intramuscular, Subcutaneous, or Intravenous (with caution).

Protect from light. Keep ampuls in tray until time of use.
Each mL contains phytonadione 10 mg; polyoxyethylated fatty acid
derivative 70 mg; dextrose, hydrous 37.5 mg; benzyl alcohol 9 mg added
as preservative. May contain hydrochloric acid for pH adjustment.
pH 6.3 (5.0 to 7.0). Usual dosage: See insert. Store at 20 to 25°C (68 to
77°F). [See USP Controlled Room Temperature.]
Distributed by Hospira, Inc.,
Lake Forest, IL 60045 USA
Novaplus is a registered
trademark of Vizient, Inc.

novaplus™

RL - 7128